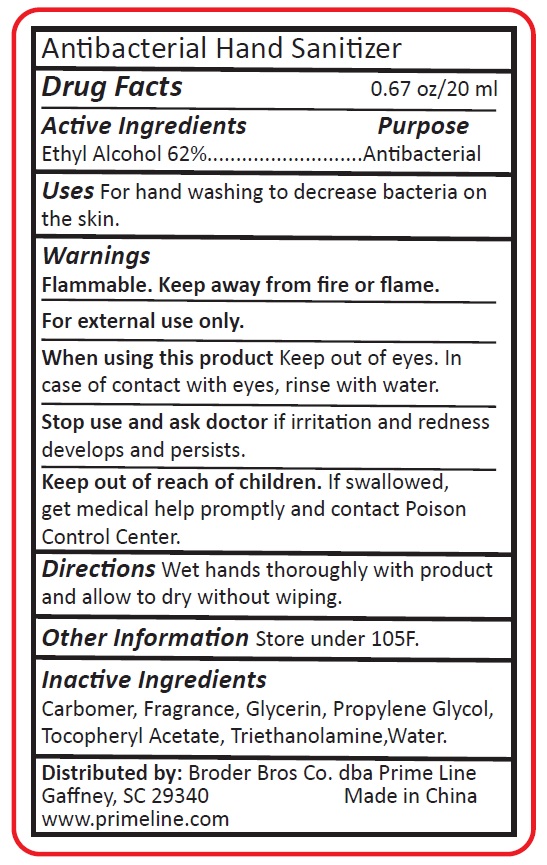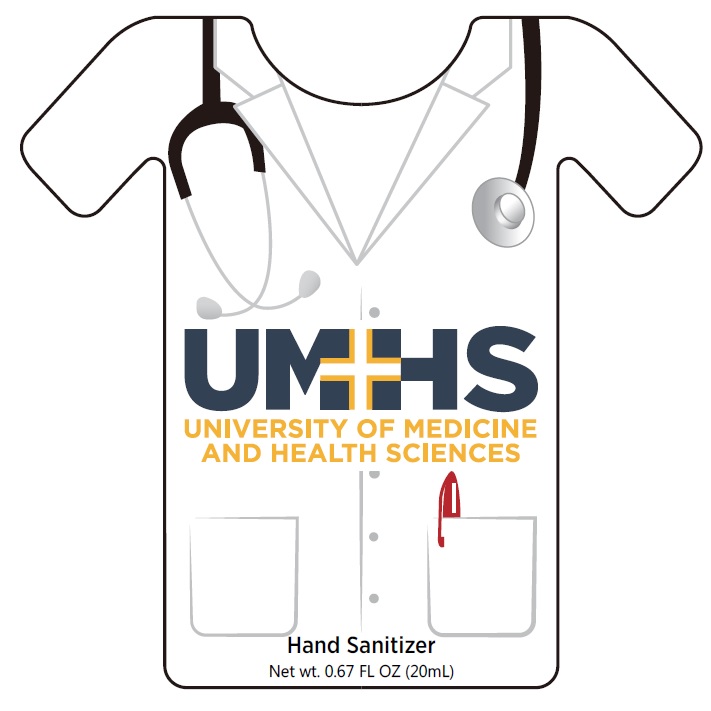 DRUG LABEL: Antibacterial Hand Sanitizer
NDC: 71513-202 | Form: SPRAY
Manufacturer: Broder Bros Co.
Category: otc | Type: HUMAN OTC DRUG LABEL
Date: 20251117

ACTIVE INGREDIENTS: ALCOHOL 62 mL/100 mL
INACTIVE INGREDIENTS: TROLAMINE; WATER; PROPYLENE GLYCOL; CARBOMER HOMOPOLYMER, UNSPECIFIED TYPE; GLYCERIN; .ALPHA.-TOCOPHEROL ACETATE; ALOE VERA LEAF

hand sanitizer spray PC187 PL1807 PL4142 PL4147

Active ingredient

Ethyl Alcohol 62%

Purpose

Antiseptic

Uses

For hand sanitizing

Warnings

- Flammable. Keep away from heat and flame.
- For external use only.

When using this product

- Keep out of eyes
- In case of contact with eyes, flush thoroughly with water
- Avoid contact with broken skin
- Do not inhale or ingest

Stop use and ask a doctor

if irritation and redness develops and persists for more than 72 hours

Keep out of reach of children

If swallowed get medical help or call a Poison Control Center right away

Directions

- Wet hands thoroughly with product, briskly rub together until dry.
- Always supervise children in use of this product.
- Children under 6 months of age: Ask a doctor.

Other information

Store at 66° to 77° F (22° to 25° C)

Inactive ingredients

Aloe Barbadensis Leaf Extract, Carbomer, Deionizer Water, Fragrance, Glycerin, Propylene Glycol, Tocopherol Acetate, Triethanolamine

Questions?

1-800-873-7746 M-F 8 am - 5 pm EST

Net wt. 10 mL/0.33 fl. oz.

Made in China

Dist. By Broder Bros Co., dba Prime Line

Gaffney, SC 29341